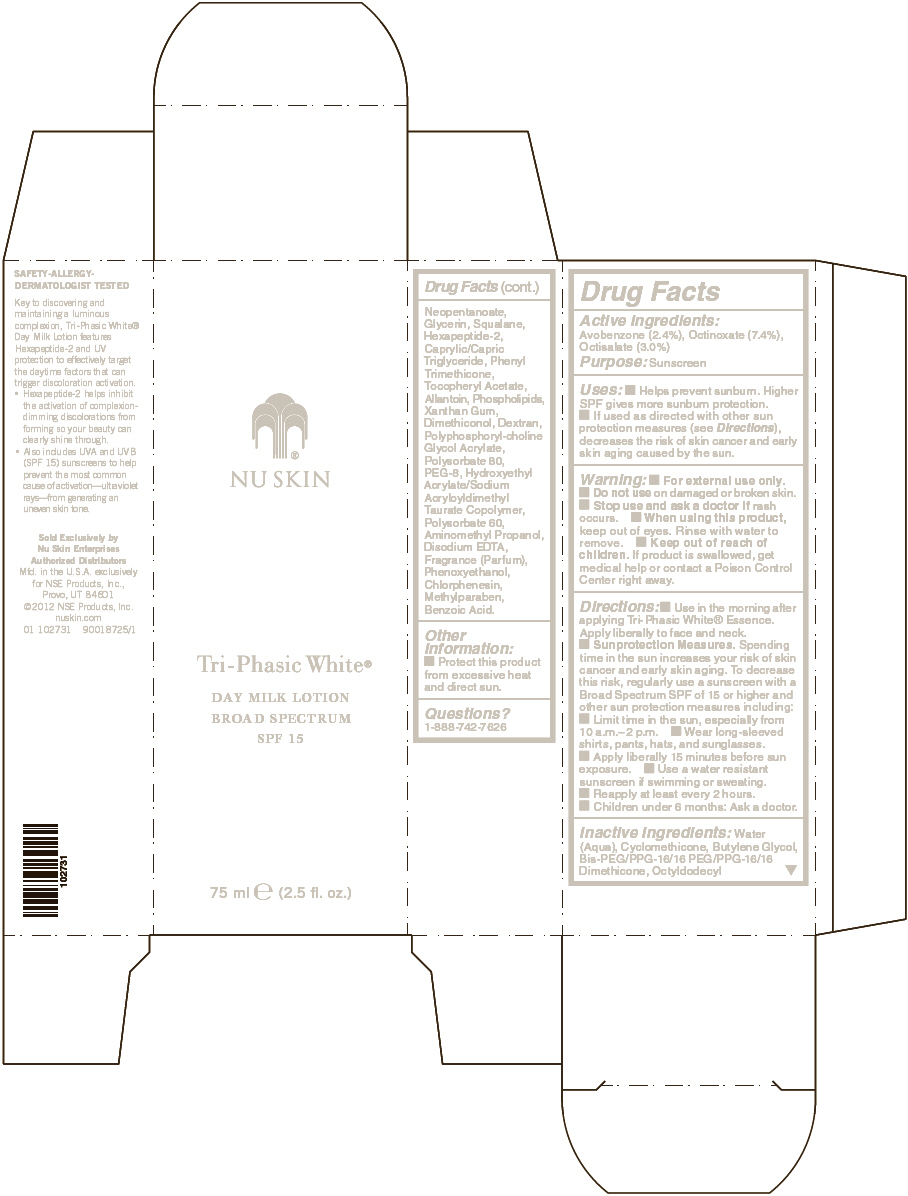 DRUG LABEL: Nu Skin Tri-Phasic White Day Milk Broad Spectrum SPF 15
NDC: 62839-0273 | Form: LOTION
Manufacturer: NSE Products, Inc.
Category: otc | Type: HUMAN OTC DRUG LABEL
Date: 20221216

ACTIVE INGREDIENTS: Avobenzone 24 mg/1 mL; Octinoxate 74 mg/1 mL; Octisalate 30 mg/1 mL
INACTIVE INGREDIENTS: Water; Cyclomethicone; Butylene Glycol; Octyldodecyl Neopentanoate; Glycerin; Squalane; Medium-Chain Triglycerides; Phenyl Trimethicone; Allantoin; Xanthan Gum; Polysorbate 80; POLYETHYLENE GLYCOL 400; Polysorbate 60; Aminomethylpropanol; Edetate Disodium; Phenoxyethanol; Chlorphenesin; Methylparaben; Benzoic Acid

NU SKIN
Tri-Phasic White®

Active Ingredients

Avobenzone (2.4%), Octinoxate (7.4%), Octisalate (3.0%).

Warnings

For external use only.

Discontinue use if irritation occurs.

Directions

Use in the morning after applying Tri-Phasic White Essence. Apply liberally to face and neck.

Inactive Ingredients

Water (Aqua), Cyclomethicone, Butylene Glycol, Bis-PEG/PPG-16/16 PEG/PPG-16/16 Dimethicone, Octyldodecyl Neopentanoate, Glycerin, Squalane, Hexapeptide-2, Caprylic/Capric Triglyceride, Phenyl Trimethicone, Tocopheryl Acetate, Allantoin, Phospholipids, Xanthan Gum, Dimethiconol, Dextran, Polyphosphorylcholine Glycol Acrylate, Polysorbate 80, PEG-8, Hydroxyethyl Acrylate/Sodium Acryloyldimethyl Taurate Copolymer, Polysorbate 60, Aminomethyl Propanol, Disodium EDTA, Fragrance (Parfum), Phenoxyethanol, Chlorphenesin, Methylparaben, Benzoic Acid.

Questions?

1-888-742-7626

PRINCIPAL DISPLAY PANEL - 75 ml Bottle Carton

NU SKIN

Tri-Phasic White®

DAY MILK LOTION
BROAD SPECTRUM
SPF 15

75 ml e (2.5 fl. oz.)